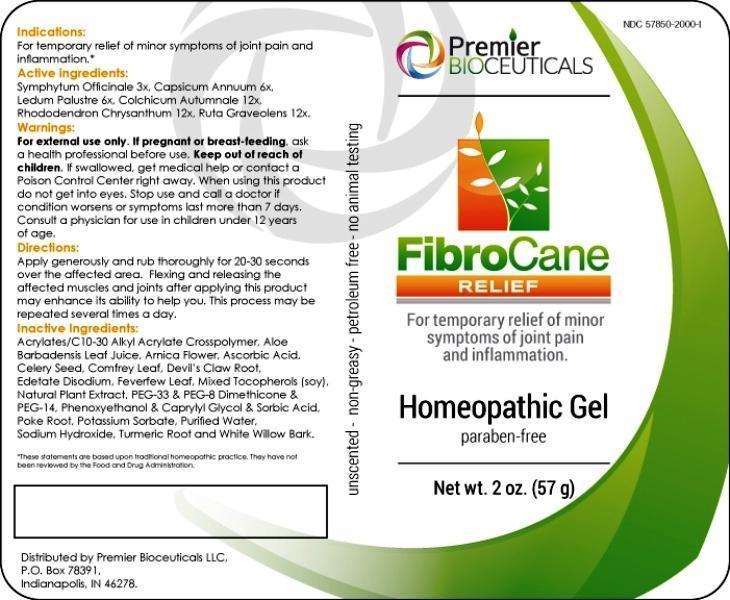 DRUG LABEL: Fibrocane Relief
NDC: 57850-2000 | Form: GEL
Manufacturer: Premier Bioceuticals LLC
Category: homeopathic | Type: HUMAN OTC DRUG LABEL
Date: 20140623

ACTIVE INGREDIENTS: COMFREY ROOT 3 [hp_X]/1 g; CAPSICUM 6 [hp_X]/1 g; LEDUM PALUSTRE TWIG 6 [hp_X]/1 g; COLCHICUM AUTUMNALE BULB 12 [hp_X]/1 g; RHODODENDRON AUREUM LEAF 12 [hp_X]/1 g; RUTA GRAVEOLENS FLOWERING TOP 12 [hp_X]/1 g
INACTIVE INGREDIENTS: CARBOMER INTERPOLYMER TYPE A (ALLYL SUCROSE CROSSLINKED); ALOE VERA LEAF; ARNICA MONTANA FLOWER; ASCORBIC ACID; CELERY SEED; COMFREY LEAF; HARPAGOPHYTUM PROCUMBENS ROOT; EDETATE DISODIUM; FEVERFEW; .ALPHA.-TOCOPHEROL; OREGANO; POLYETHYLENE GLYCOL 1500; PEG-8 DIMETHICONE; POLYETHYLENE GLYCOL 700; PHENOXYETHANOL; CAPRYLYL GLYCOL; SORBIC ACID; PHYTOLACCA AMERICANA ROOT; POTASSIUM SORBATE; WATER; SODIUM HYDROXIDE; TURMERIC; SALIX ALBA BARK

Drug Facts

ACTIVE INGREDIENTS:

Symphytum officinale 3X, Capsicum annuum 6X, Ledum palustre 6X, Colchicum autumnale 12X, Rhododendron chrysanthum 12X, Ruta graveolens 12X.

INDICATIONS:

For temporary relief of minor symptoms of joint pain and inflammation.*

*These statements are based upon traditional homeopathic practice. They have not been reviewed by the Food and Drug Administration.

WARNINGS:

For external use only.

If pregnant or breast-feeding, ask a health professional before use.

Keep out of reach of children. If swallowed, get medical help or contact a Poison Control Center right away.

When using this product do not get into eyes.

Stop use and call a doctor if condition worsens or symptoms last more than 7 days.

Consult a physician for use in children under 12 years of age.

Keep out of reach of children. If swallowed, get medical help or contact a Poison Control Center right away.

DIRECTIONS:

Apply generously and rub thoroughly for 20-30 seconds over the affected area. Flexing and releasing the affected muscles and joints after applying this product may enhance its ability to help you. This process may be repeated several times a day.

INDICATIONS:

For temporary relief of minor symptoms of joint pain and inflammation.*

*These statements are based upon traditional homeopathic practice. They have not been reviewed by the Food and Drug Administration.

INACTIVE INGREDIENTS:

Acrylates/C10-30 alkyl acrylate crosspolymer, Aloe barbadensis leaf juice, Arnica (flower), Ascorbic acid, Celery (seed), Comfrey leaf, Devil's Claw (root), Edate disodium (EDTA), Feverfew (leaf), Vitamin E, Oregano, PEG-33, PEG-8 Dimethicone, PEG-14, Phenoxyethanol, Capryly glycol, Sorbic acid, Poke (root), Potassium sorbate, Purified Water, Sodium hydroxide, Turmeric (root), White willow (bark)

QUESTIONS:

Distributed by Premier Bioceuticals LLC,

P. O. BOX 78391

Indianapolis, IN 46278

PACKAGE LABEL DISPLAY:

Premier BIOCEUTICALS

NDC 57850-2000-1

FibroCane

RELIEF

For temporary relief of monor symptoms of joint pain and inflammation.

Homeopathic Gel

paraben-free

Ner wt. 2 oz. (57 g)